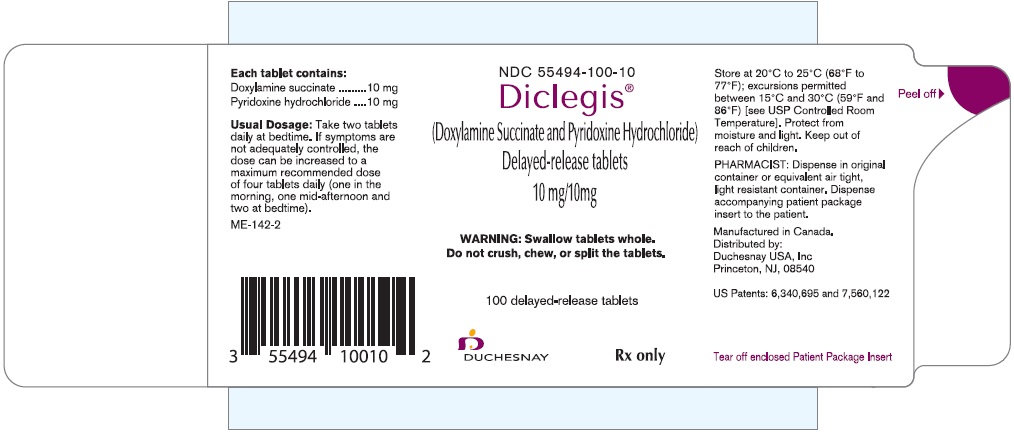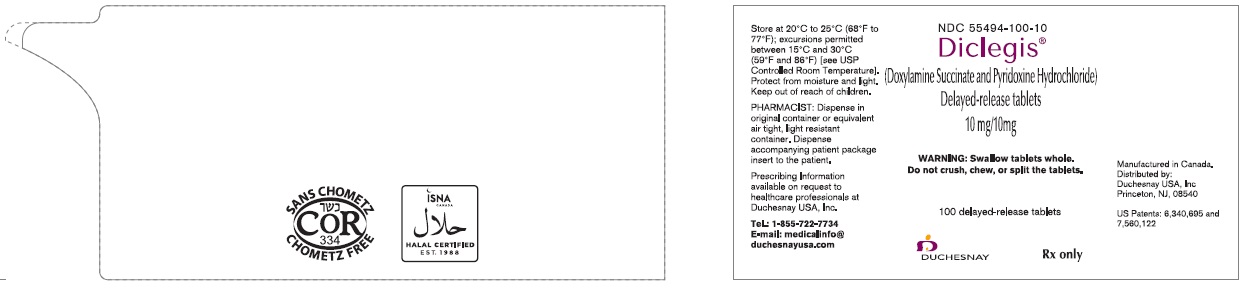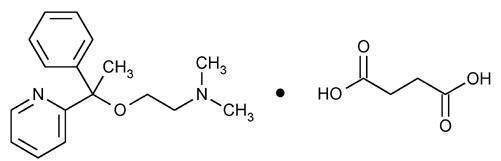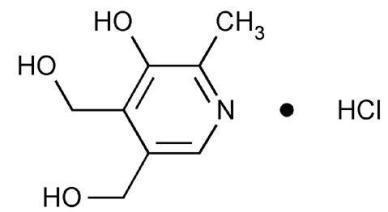 DRUG LABEL: DICLEGIS
NDC: 55494-100 | Form: TABLET, DELAYED RELEASE
Manufacturer: Duchesnay USA, Inc.
Category: prescription | Type: HUMAN PRESCRIPTION DRUG LABEL
Date: 20251203

ACTIVE INGREDIENTS: DOXYLAMINE SUCCINATE 10 mg/1 1; PYRIDOXINE HYDROCHLORIDE 10 mg/1 1
INACTIVE INGREDIENTS: AMMONIA; BUTYL ALCOHOL; SILICON DIOXIDE; CROSCARMELLOSE SODIUM; D&C RED NO. 27; FD&C BLUE NO. 2; HYPROMELLOSES; ISOPROPYL ALCOHOL; MAGNESIUM STEARATE; MAGNESIUM TRISILICATE; POLYETHYLENE GLYCOL 400; POLYETHYLENE GLYCOL 8000; POLYSORBATE 80; PROPYLENE GLYCOL; TALC; TITANIUM DIOXIDE; CELLULOSE, MICROCRYSTALLINE; CARNAUBA WAX; ALCOHOL; METHACRYLIC ACID - ETHYL ACRYLATE COPOLYMER (1:1) TYPE A; SHELLAC; DIMETHICONE; SODIUM BICARBONATE; SODIUM LAURYL SULFATE; TRIETHYL CITRATE

HIGHLIGHTS OF PRESCRIBING INFORMATION

These highlights do not include all the information needed to use DICLEGIS safely and effectively. See full prescribing information for DICLEGIS.
DICLEGIS (doxylamine succinate and pyridoxine hydrochloride) delayed-release tablets, for oral use.
Initial U.S. Approval: 1976

RECENT MAJOR CHANGES

Warnings and Precautions, Concomitant Medical Conditions (5.2) 10/2022

1 INDICATIONS AND USAGE

DICLEGIS is a fixed dose combination drug product of doxylamine succinate, an antihistamine, and pyridoxine hydrochloride, a Vitamin B6 analog, indicated for the treatment of nausea and vomiting of pregnancy in women who do not respond to conservative management. (1)

2 DOSAGE AND ADMINISTRATION

Take two tablets daily at bedtime. If symptoms are not adequately controlled, the dose can be increased to a maximum recommended dose of four tablets daily (one in the morning, one mid-afternoon and two at bedtime) as described in the full prescribing information. (2)

3 DOSAGE FORMS AND STRENGTHS

Delayed-release tablets containing 10 mg doxylamine succinate and 10 mg pyridoxine hydrochloride. (3)

4 CONTRAINDICATIONS

- Known hypersensitivity to doxylamine succinate, other ethanolamine derivative antihistamines, pyridoxine hydrochloride or any inactive ingredient in the formulation (4)
- Monoamine oxidase (MAO) inhibitors (4, 7)

5 WARNINGS AND PRECAUTIONS

- Activities requiring mental alertness: Avoid engaging in activities requiring complete mental alertness, such as driving or operating heavy machinery, while using DICLEGIS until cleared to do so by a healthcare provider (5.1)
- Central nervous system (CNS) depressants: Concurrent use with alcohol or other CNS depressants is not recommended (5.1)
- Anticholinergic actions: Use with caution in patients with increased intraocular pressure, narrow angle glaucoma, stenosing peptic ulcer, pyloroduodenal obstruction and urinary bladder-neck obstruction (5.2)
- Interference with urine drug screen: DICLEGIS may interfere with urine screening for methadone, opiates and PCP (5.3)

6 ADVERSE REACTIONS

The most common adverse reaction with DICLEGIS (≥5 percent and exceeding the rate in placebo) is somnolence. (6)

To report SUSPECTED ADVERSE REACTIONS, contact Duchesnay Inc. at 1-855-722-7734 or medicalinfo@duchesnayusa.com or FDA at 1-800-FDA-1088 or www.fda.gov/medwatch.

7 DRUG INTERACTIONS

- Severe drowsiness can occur when used in combination with alcohol or other sedating medications. (7)

8 USE IN SPECIFIC POPULATIONS

DICLEGIS is intended for use in pregnant women. (8.1)

FULL PRESCRIBING INFORMATION

1 INDICATIONS AND USAGE

DICLEGIS is indicated for the treatment of nausea and vomiting of pregnancy in women who do not respond to conservative management.

Limitations of Use

DICLEGIS has not been studied in women with hyperemesis gravidarum.

2 DOSAGE AND ADMINISTRATION

2.1 Dosage Information

Initially, take two DICLEGIS delayed-release tablets orally at bedtime (Day 1). If this dose adequately controls symptoms the next day, continue taking two tablets daily at bedtime. However, if symptoms persist into the afternoon of Day 2, take the usual dose of two tablets at bedtime that night then take three tablets starting on Day 3 (one tablet in the morning and two tablets at bedtime). If these three tablets adequately control symptoms on Day 4, continue taking three tablets daily. Otherwise take four tablets starting on Day 4 (one tablet in the morning, one tablet mid-afternoon and two tablets at bedtime).

The maximum recommended dose is four tablets (one in the morning, one in the mid-afternoon and two at bedtime) daily.

Take on an empty stomach with a glass of water [see Clinical Pharmacology (12.3)]. Swallow tablets whole. Do not crush, chew, or split DICLEGIS tablets.

Take as a daily prescription and not on an as needed basis. Reassess the woman for continued need for DICLEGIS as her pregnancy progresses.

3 DOSAGE FORMS AND STRENGTHS

DICLEGIS delayed-release tablets are white, round, film coated tablets containing 10 mg doxylamine succinate and 10 mg pyridoxine hydrochloride. The tablets are imprinted with the pink image of a pregnant woman on one side.

4 CONTRAINDICATIONS

DICLEGIS is contraindicated in women with any of the following conditions:

- Known hypersensitivity to doxylamine succinate, other ethanolamine derivative antihistamines, pyridoxine hydrochloride or any inactive ingredient in the formulation
- Monoamine oxidase (MAO) inhibitors intensify and prolong the adverse central nervous system effects of DICLEGIS [see Drug Interactions (7.1)].

5 WARNINGS AND PRECAUTIONS

5.1 Activities Requiring Mental Alertness

DICLEGIS may cause somnolence due to the anticholinergic properties of doxylamine succinate, an antihistamine. Women should avoid engaging in activities requiring complete mental alertness, such as driving or operating heavy machinery, while using DICLEGIS until cleared to do so by their healthcare provider.

DICLEGIS use is not recommended if a woman is concurrently using central nervous system (CNS) depressants including alcohol. The combination may result in severe drowsiness leading to falls or accidents [see Drug Interactions (7.1)].

5.2 Concomitant Medical Conditions

DICLEGIS has anticholinergic properties and, therefore, should be used with caution in women with: increased intraocular pressure, narrow angle glaucoma, stenosing peptic ulcer, pyloroduodenal obstruction and urinary bladder-neck obstruction.

5.3 Interference with Urine Screen for Methadone, Opiates and Phencyclidine Phosphate (PCP)

There have been reports of false positive urine screening tests for methadone, opiates, and PCP with doxylamine succinate/pyridoxine hydrochloride use [see Drug Interactions (7.3)].

6 ADVERSE REACTIONS

The following adverse reactions are discussed elsewhere in the labeling:

- Somnolence [see Warnings and Precautions (5.1)]
- Falls or other accidents resulting from the effect of the combined use of DICLEGIS with CNS depressants including alcohol [see Warnings and Precautions (5.1)]

6.1 Clinical Trial Experience

Because clinical trials are conducted under widely varying conditions, adverse reaction rates observed in the clinical trials of a drug cannot be directly compared to rates in the clinical trials of another drug and may not reflect the rates observed in clinical practice.

The safety and efficacy of DICLEGIS were compared to placebo in a double-blind, randomized, multi-center trial in 261 women with nausea and vomiting of pregnancy. The mean gestational age at enrollment was 9.3 weeks, range 7 to 14 weeks gestation [see Clinical Studies (14)]. Adverse reactions for DICLEGIS that occurred at an incidence ≥5 percent and exceeded the incidence for placebo are summarized in Table 1.

Table 1: Number (Percent) of Subjects with ≥ 5 Percent Adverse Reactions in a 15‑Day Placebo-Controlled Study of DICLEGIS (Only Those Adverse Reactions Occurring at an Incidence ≥ 5 Percent and at a Higher Incidence with DICLEGIS than Placebo are Shown)

 | Diclegis; (N = 133) | Placebo; (n = 128)
Somnolence | 19 (14.3%) | 15 (11.7%)

6.2 Postmarketing Experience

The following adverse events, listed alphabetically, have been identified during post-approval use of the combination of 10 mg doxylamine succinate and 10 mg pyridoxine hydrochloride. Because these reactions are reported voluntarily from a population of uncertain size, it is not always possible to reliably estimate their frequency or establish a causal relationship to drug exposure.

Cardiac disorders: dyspnea, palpitation, tachycardia

Ear and labyrinth disorders: vertigo

Eye disorders: vision blurred, visual disturbances

Gastrointestinal disorders: abdominal distension, abdominal pain, constipation, diarrhea

General disorders and administration site conditions: chest discomfort, fatigue, irritability, malaise

Immune system disorders: hypersensitivity

Nervous system disorders: dizziness, headache, migraines, paresthesia, psychomotor hyperactivity

Psychiatric disorders: anxiety, disorientation, insomnia, nightmares

Renal and urinary disorders: dysuria, urinary retention

Skin and subcutaneous tissue disorders: hyperhidrosis, pruritus, rash, rash maculo-papular

7 DRUG INTERACTIONS

7.1 Drug Interactions

Use of DICLEGIS is contraindicated in women who are taking monoamine oxidase inhibitors (MAOIs), which prolong and intensify the anticholinergic (drying) effects of antihistamines. Concurrent use of alcohol and other CNS depressants (such as hypnotic sedatives and tranquilizers) with DICLEGIS is not recommended.

7.2 Drug-Food Interactions

A food-effect study demonstrated that the delay in the onset of action of DICLEGIS may be further delayed, and a reduction in absorption may occur when tablets are taken with food [see Dosage and Administration (2), Clinical Pharmacology (12.3)]. Therefore, DICLEGIS should be taken on an empty stomach with a glass of water [see Dosage and Administration (2)].

7.3 False Positive Urine Tests for Methadone, Opiates and PCP

False positive drug screens for methadone, opiates, and PCP can occur with doxylamine succinate/pyridoxine hydrochloride use. Confirmatory tests, such as Gas Chromatography Mass Spectrometry (GC-MS), should be used to confirm the identity of the substance in the event of a positive immunoassay result.

8 USE IN SPECIFIC POPULATIONS

8.1 Pregnancy

Risk Summary

DICLEGIS is intended for the treatment of nausea and vomiting of pregnancy in women who do not respond to conservative management. Maternal risks are discussed throughout the labeling. No increased risk for congenital malformations has been reported in epidemiologic studies in pregnant women.

In the U.S. general population, the estimated background risks for major birth defects and miscarriage in clinically recognized pregnancies are 2-4% and 15-20%, respectively.

Data

Human Data

The combination of doxylamine succinate and pyridoxine hydrochloride has been the subject of many epidemiological studies (cohort, case control and meta-analyses) designed to detect possible teratogenicity. A meta-analysis of 16 cohort and 11 case-control studies published between 1963 and 1991 reported no increased risk for malformations from first trimester exposures to doxylamine succinate and pyridoxine hydrochloride, with or without dicyclomine hydrochloride. A second meta-analysis of 12 cohort and 5 case-control studies published between 1963 and 1985 reported no statistically significant relationships between fetal abnormalities and the first trimester use of the combination doxylamine succinate and pyridoxine hydrochloride with or without dicyclomine hydrochloride.

8.2 Lactation

Women should not breastfeed while using DICLEGIS.

The molecular weight of doxylamine succinate is low enough that passage into breast milk can be expected. Excitement, irritability and sedationhave been reported in nursing infants presumably exposed to doxylamine succinate through breast milk. Infants with apnea or other respiratory syndromes may be particularly vulnerable to the sedative effects of DICLEGIS resulting in worsening of their apnea or respiratory conditions.

Pyridoxine hydrochloride is excreted into breast milk. There have been no reports of adverse events in infants presumably exposed to pyridoxine hydrochloride through breast milk.

8.4 Pediatric Use

The safety and effectiveness of DICLEGIS in children under 18 years of age have not been established.

Fatalities have been reported from doxylamine overdose in children. The overdose cases have been characterized by coma, grand mal seizures and cardiorespiratory arrest. Children appear to be at a high risk for cardiorespiratory arrest. A toxic dose for children of more than 1.8 mg/kg has been reported. A 3 year old child died 18 hours after ingesting 1,000 mg doxylamine succinate. However, there is no correlation between the amount of doxylamine ingested, the doxylamine plasma level and clinical symptomatology.

10 OVERDOSAGE

10.1 Signs and Symptoms of Overdose

DICLEGIS is a delayed-release formulation, therefore, signs and symptoms of intoxication may not be apparent immediately.

Signs and symptoms of overdose may include restlessness, dryness of mouth, dilated pupils, sleepiness, vertigo, mental confusion and tachycardia.

At toxic doses, doxylamine exhibits anticholinergic effects, including seizures, rhabdomyolysis, acute renal failure and death.

10.2 Management of Overdose

If treatment is needed, it consists of gastric lavage or activated charcoal, whole bowel irrigation and symptomatic treatment. For additional information about overdose treatment, call a poison control center (1‑800-222-1222).

11 DESCRIPTION

DICLEGIS (doxylamine succinate and pyridoxine hydrochloride) delayed-release tablets are round, white, film-coated, delayed-release tablets containing 10 mg of doxylamine succinate and 10 mg of pyridoxine hydrochloride. Tablets are imprinted on one side with the pink image of a pregnant woman.

Inactive ingredients are as follows: ammonium hydroxide, n-butanol, carnauba wax powder, colloidal silicon dioxide, croscarmellose sodium, D&C Red#27, denatured alcohol, FD&C Blue#2, hypromellose, isopropyl alcohol, magnesium stearate, magnesium trisilicate, methacrylic acid copolymer, microcrystalline cellulose 102, PEG 400, PEG 8000, polysorbate 80, propylene glycol, shellac glaze, simethicone, sodium bicarbonate, sodium lauryl sulfate, talc, titanium dioxide, triethyl citrate.

Doxylamine Succinate

Doxylamine succinate is classified as an antihistamine. The chemical name for doxylamine succinate is ethanamine, N,N-dimethyl-2-[1-phenyl-1-(2-pyridinyl)ethoxy]-, butanedioate (1:1). The empirical formula is C17H22N2O • C4H6O4 and the molecular mass is 388.46. The structural formula is:

Doxylamine succinate is a white to creamy white powder that is very soluble in water and alcohol, freely soluble in chloroform and very slightly soluble in ether and benzene.

Pyridoxine Hydrochloride

Pyridoxine hydrochloride is a vitamin B6 analog. The chemical name for pyridoxine hydrochloride is 3,4-pyridinedimethanol, 5-hydroxy-6-methyl-, hydrochloride. The empirical formula is C8H11NO3 • HCl and the molecular mass is 205.64. The structural formula is:

Pyridoxine hydrochloride is a white or practically white crystalline powder that is freely soluble in water, slightly soluble in alcohol and insoluble in ether.

12 CLINICAL PHARMACOLOGY

12.1 Mechanism of Action

The mechanism of action of DICLEGIS is unknown.

12.3 Pharmacokinetics

The pharmacokinetics of DICLEGIS has been characterized in healthy non-pregnant adult women. Pharmacokinetic results for doxylamine and pyridoxine, including its vitamin B6 metabolites, pyridoxal, pyridoxal 5’-phosphate, pyridoxamine and pyridoxamine 5’-phosphate, are summarized in Tables 2 to 5.

Absorption

A single-dose (two tablets) and multiple-dose (four tablets daily), open-label study was conducted to assess the safety and pharmacokinetic profile of DICLEGIS administered in healthy non-pregnant adult women. Single-doses (two tablets at bedtime) were administered on Days 1 and 2. Multiple-doses (one tablet in the morning, one tablet in the afternoon and two tablets at bedtime) were administered on Days 3-18.

Blood samples for pharmacokinetic analysis were collected pre-and post-dose on Days 2 and 18 as well as pre-dose prior to bedtime dose only (trough) on Days 9, 10, 11, 16, 17, and 18.

Doxylamine and pyridoxine are absorbed in the gastrointestinal tract, mainly in the jejunum.

The Cmax of doxylamine and pyridoxine are achieved within 7.5 and 5.5 hours, respectively (see Table 2).

Table 2 – Single-Dose and Multiple-Dose Pharmacokinetics of DICLEGIS in Healthy Non-Pregnant Adult Women
 | Single Dose |  |  | Multiple Dose
 | AUC0-inf | Cmax | Tmax | AUC0-inf | Cmax | Tmax
 | (ng•h/mL) | (ng/mL) | (h) | (ng•h/mL) | (ng/mL) | (h)
Doxylamine | 1280.9 ± 369.3 | 83.3 ± 20.6 | 7.2 ± 1.9 | 3721.5 ± 1318.5 | 168.6 ± 38.5 | 7.8 ± 1.6
Pyridoxine | 43.4 ± 16.5 | 32.6 ± 15.0 | 5.7 ± 1.5 | 64.5 ± 36.4 | 46.1 ± 28.3 | 5.6 ± 1.3
Pyridoxal | 211.6 ± 46.1 | 74.3 ± 21.8 | 6.5 ± 1.4 | 1587.2 ± 550.0 | 210.0 ± 54.4 | 6.8 ± 1.2
Pyridoxal 5`Phosphate | 1536.4 ± 721.5 | 30.0 ± 10.0 | 11.7 ± 5.3 | 6099.7 ± 1383.7 | 84.9 ± 16.9 | 6.3 ± 6.6
Pyridoxamine | 4.1 ± 2.7 | 0.5 ± 0.7 | 5.9 ± 2.1 | 2.6 ± 0.8 | 0.5 ± 0.2 | 6.6 ± 1.4
Pyridoxamine 5'-phosphate | 5.2 ± 3.8 | 0.7 ± 0.5 | 14.8 ± 6.6 | 94.5 ± 58.0 | 2.3 ± 1.7 | 12.4 ± 11.2

Multiple-dose administration of DICLEGIS results in increased concentrations of doxylamine as well as increases in doxylamine Cmax and AUC0-last of absorption. The time to reach the maximum concentration is not affected by multiple doses. The mean accumulation index is more than 1.0 suggesting that doxylamine accumulates following multiple dosing (see Table 3).

Although no accumulation was observed for pyridoxine, the mean accumulation index for each metabolite (pyridoxal, pyridoxal 5’-phosphate, and pyridoxamine 5’-phosphate) is more than 1.0 following multiple-dose administration of DICLEGIS. The time to reach the maximum concentration is not affected by multiple doses (see Table 2).

Table 3 – Pharmacokinetics of Doxylamine and Pyridoxine Following Single Dose and Multiple Dose Administration of DICLEGIS to Healthy Non-Pregnant Adult Women
 |  | AUC0-last (ng•h/mL) | AUC0-inf (ng•h/mL) | Cmax (ng/mL) | Tmax (h) | T1/2el (h)
Doxylamine Mean±SD N=18 | Single | 911.4 ± 205.6 | 1280.9 ± 369.3 | 83.3 ± 20.6 | 7.2 ± 1.9 | 10.1 ± 2.1
Doxylamine Mean±SD N=18 | Multiple | 3661.3 ± 1279.2 | 3721.5 ± 1318.5 | 168.6 ± 38.5 | 7.8 ± 1.6 | 11.9 ± 3.3
Pyridoxine Mean±SD N=18 | Single | 39.3 ± 16.5 | 43.4 ± 16.5 | 32.6 ± 15.0 | 5.7 ± 1.5 | 0.5 ± 0.2
Pyridoxine Mean±SD N=18 | Multiple | 59.3 ± 33.9 | 64.5 ± 36.4 | 46.1 ± 28.3 | 5.6 ± 1.3 | 0.5 ± 0.1

Food Effect

The administration of food delays the absorption of both doxylamine and pyridoxine. This delay is associated with a lower peak concentration of doxylamine, but the extent of absorption is not affected (see Table 4).

The effect of food on the peak concentration and the extent of absorption of the pyridoxine component is more complex because the pyridoxal, pyridoxamine, pyridoxal 5’-phosphate and pyridoxamine 5’-phosphate metabolites also contribute to the biological activity. Food significantly reduces the bioavailability of pyridoxine, lowering its Cmax and AUC by approximately 50% compared to fasting conditions. Similarly, food significantly reduces pyridoxal AUC and reduces its Cmax by 50% compared to fasting conditions. In contrast, food slightly increases pyridoxal 5’-phosphate Cmax and extent of absorption. As for pyridoxamine and pyridoxamine 5’-phosphate, the rate and extent of absorption seem to decrease under fed conditions.

Table 4 – Pharmacokinetics of Doxylamine and Pyridoxine Following Administration of DICLEGIS Under Fed and Fasted Conditions in Healthy Non-Pregnant Adult Women
 |  | AUC0-t (ng•h/mL) | AUC0-inf (ng•h/mL) | Cmax (ng/mL) | Tmax (h) | T1/2el (h)
Doxylamine Mean±SD N=42 | Fasted | 1407.2 ± 336.9 | 1447.9 ± 332.2 | 94.9 ± 18.4 | 5.1 ± 3.4 | 12.6 ± 3.4
Doxylamine Mean±SD N=42 | Fed | 1488.0 ± 463.2 | 1579.0 ± 422.7 [N=37] | 75.7 ± 16.6 | 14.9 ± 7.4 | 12.5 ± 2.9
Pyridoxine Mean±SD N=42 | Fasted | 33.8 ± 13.7 | 39.5 ± 12.9 [N=31] | 35.5 ± 21.4 | 2.5 ± 0.9 | 0.4 ± 0.2
Pyridoxine Mean±SD N=42 | Fed | 18.3 ± 14.5 | 24.2 ±14.0 [N=18] | 13.7 ± 10.8 | 9.3 ± 4.0 | 0.5 ± 0.2

Distribution

Pyridoxine is highly protein bound, primarily to albumin. Its main active metabolite, pyridoxal 5’-phosphate (PLP) accounts for at least 60% of circulating vitamin B6 concentrations.

Metabolism

Doxylamine is biotransformed in the liver by N-dealkylation to its principal metabolites N-desmethyl-doxylamine and N, N-didesmethyldoxylamine.

Pyridoxine is a prodrug primarily metabolized in the liver.

Excretion

The principal metabolites of doxylamine, N-desmethyl-doxylamine and N, N-didesmethyldoxylamine, are excreted by the kidney.

The terminal elimination half-life of doxylamine and pyridoxine are 12.5 hours and 0.5 hours, respectively (see Table 5).

Table 5 – Terminal Elimination Half-Life (T1/2el) for DICLEGIS Administered as a Single Dose of Two Tablets under Fasting Conditions in Healthy Non-Pregnant Adult Women

 | T1/2el (h)
Doxylamine | 12.6 ± 3.4
Pyridoxine | 0.4 ± 0.2
Pyridoxal | 2.1 ± 2.2
Pyridoxal 5’-Phosphate | 81.6 ± 42.2
Pyridoxamine | 3.1 ± 2.5
Pyridoxamine 5’-Phosphate | 66.5 ± 51.3

Use in Specific Populations

Race: No pharmacokinetic studies have been conducted related to race.

Hepatic Impairment: No pharmacokinetic studies have been conducted in hepatic impaired patients.

Renal Impairment: No pharmacokinetic studies have been conducted in renal impaired patients.

13 NONCLINICAL TOXICOLOGY

13.1 Carcinogenesis, Mutagenesis and Impairment of Fertility

Carcinogenicity

Two-year carcinogenicity studies in rats and mice have been conducted with doxylamine succinate. Doxylamine succinate is not likely to have human carcinogenic potential. The carcinogenic potential of pyridoxine hydrochloride has not been evaluated.

14 CLINICAL STUDIES

A double-blind, randomized, multi-center, placebo-controlled study was conducted to support the safety and efficacy of DICLEGIS in the treatment of nausea and vomiting of pregnancy. Adult women 18 years of age or older and 7 to 14 weeks gestation (median 9 weeks of gestation) with nausea and vomiting of pregnancy were randomized to 14 days of DICLEGIS or placebo. Two tablets of DICLEGIS were administered at bedtime on Day 1. If symptoms of nausea and vomiting persisted into the afternoon hours of Day 2, the woman was directed to take her usual dose of two tablets at bedtime that night and, beginning on Day 3, to take one tablet in the morning and two tablets at bedtime. Based upon assessment of remaining symptoms at her clinic visit on Day 4 (± 1 day), the woman may have been directed to take an additional tablet mid-afternoon. A maximum of four tablets (one in the morning, one in the mid-afternoon and two at bedtime) were taken daily.

Over the treatment period, 19% of DICLEGIS-treated patients remained on 2 tablets daily, 21% received 3 tablets daily, and 60% received 4 tablets daily.

The primary efficacy endpoint was the change from baseline at Day 15 in the Pregnancy Unique-Quantification of Emesis (PUQE) score. The PUQE score incorporates the number of daily vomiting episodes, number of daily heaves, and length of daily nausea in hours, for an overall score of symptoms rated from 3 (no symptoms) to 15 (most severe).

At baseline, the mean PUQE score was 9.0 in the DICLEGIS arm and 8.8 in the placebo arm. There was a 0.7 (95% confidence interval 0.2 to 1.2 with p-value 0.006) mean decrease (improvement in nausea and vomiting symptoms) from baseline in PUQE score at Day 15 with DICLEGIS compared to placebo (see Table 6).

Table 6 – Change from Baseline in the Primary Endpoint, Pregnancy Unique-Quantification of Emesis (PUQE) Score at Day 15. (Intent-to-Treat Population with Last-Observation Carried Forward)

PUQE Score [The Pregnancy-Unique Quantification of Emesis and Nausea (PUQE) score incorporated the number of daily vomiting episodes, number of daily heaves, and length of daily nausea in hours, for an overall score of symptoms rated from 3 (no symptoms) to 15 (most severe). Baseline was defined as the PUQE score completed at the enrollment visit.] | Doxylamine Succinate + Pyridoxine Hydrochloride | Placebo | Treatment Difference [95% Confidence Interval]
Baseline Change from baseline at Day 15 | 9.0 ± 2.1 -4.8 ± 2.7 | 8.8 ± 2.1 -3.9 ± 2.6 | -0.7 [-1.2, -0.2]

16 HOW SUPPLIED/STORAGE AND HANDLING

16.1 How supplied

DICLEGIS delayed-release tablets are supplied in a high-density polyethylene bottle with a polypropylene child-resistant cap and a silica gel desiccant canister. Each white, round, film-coated, delayed-release tablet contains 10 mg doxylamine succinate and 10 mg pyridoxine hydrochloride, and is imprinted on one side with the pink image of a pregnant woman. DICLEGIS tablets are provided as follows:

NDC 55494-100-10 Bottles of 100.

16.2 Storage and Handling

Store at 20°C to 25°C (68°F to 77°F); excursions permitted between 15°C and 30°C (59°F and 86°F) [see USP Controlled Room Temperature]. Keep bottle tightly closed and protect from moisture. Do not remove desiccant canister from bottle.

17 PATIENT COUNSELING INFORMATION

See FDA-approved patient labeling (Patient Information)

Somnolence and Severe Drowsiness

Inform women to avoid engaging in activities requiring complete mental alertness, such as driving or operating heavy machinery, while using DICLEGIS until cleared to do so.

Inform women of the importance of not taking DICLEGIS with alcohol or sedating medications, including other antihistamines (present in some cough and cold medications), opiates and sleep aids because somnolence could worsen leading to falls or other accidents.

Interference with urine drug screening

Inform women that use of DICLEGIS may result in false positive urine drug screening for methadone, opiates and PCP.

DICLEGIS® is a registered trademark of Duchesnay Inc.

U.S. Patent Nos. 6,340,695 & 7,560,122.

Distributed by:
Duchesnay USA, Inc.
Princeton, NJ 08540
Tel: 1-855-722-7734
Fax: 1-888-588-8508
www.duchesnayusa.com

©2018, Duchesnay Inc. All rights reserved.

Patient Package Insert

Patient Information

DICLEGIS (dye-CLEE-gis)

(doxylamine succinate and pyridoxine hydrochloride) delayed-release tablets

What is DICLEGIS?

- DICLEGIS is a prescription medicine used to treat nausea and vomiting of pregnancy in women who have not improved with change in diet or other non-medicine treatments.
- It is not known if DICLEGIS is safe and effective in women with severe nausea and vomiting of pregnancy, a condition called hyperemesis gravidarum. Women with this condition may need to be hospitalized.
- It is not known if DICLEGIS is safe and effective in children under 18 years of age.

Who should not take DICLEGIS?

Do not take DICLEGIS if you:

- are allergic to doxylamine succinate, other ethanolamine derivative antihistamines, pyridoxine hydrochloride or any of the ingredients in DICLEGIS. See the end of this leaflet for a complete list of ingredients in DICLEGIS.
- take monoamine oxidase inhibitors (MAOIs). Ask your healthcare provider or pharmacist if you are not sure if you take an MAOI, including Marplan, Nardil, Emsam, Eldepryl, Zelapar, and Parnate.

Before taking DICLEGIS, tell your healthcare provider about all of your medical conditions, including if you:

- have eye problems called increased intraocular pressure or narrow angle glaucoma.
- have a stomach problem called stenosing peptic ulcer or pyloroduodenal obstruction.
- have a bladder problem called urinary bladder-neck obstruction.
- are breastfeeding or plan to breastfeed. DICLEGIS can pass into your breast milk and may harm your baby. You should not breastfeed while using DICLEGIS.

Tell your healthcare provider about all the medicines you take, including prescription or over-the-counter medicines, vitamins, or herbal supplements.

How should I take DICLEGIS?

- Talk to your healthcare provider about how much DICLEGIS to take and when to take it.
- Take DICLEGIS everyday as prescribed by your healthcare provider. Do not stop taking DICLEGIS without talking to your healthcare provider first.
- See the following schedule for the usual way you should start taking DICLEGIS:
  - Day 1- Take 2 tablets, by mouth at bedtime.
  - Day 2- Take 2 tablets at bedtime. If your nausea and vomiting is better or controlled on Day 2, continue to take 2 tablets every night at bedtime. This will be your usual dose unless your healthcare provider tells you otherwise.
  - Day 3- If you still had nausea and vomiting on Day 2, take 3 tablets on Day 3 (1 tablet in the morning and 2 tablets at bedtime).
  - Day 4- If your nausea and vomiting was better or controlled on Day 3, continue to take 3 tablets each day (1 tablet in the morning and 2 tablets at bedtime). If you still had nausea and vomiting on Day 3, start taking 4 tablets each day (1 tablet in the morning, 1 tablet in the afternoon, and 2 tablets at bedtime).
- Do not take more than 4 tablets (1 in the morning, 1 in the mid-afternoon, and 2 at bedtime) in 1 day.
- Take DICLEGIS on an empty stomach with a glass of water.
- Take DICLEGIS tablets whole. Do not crush, chew, or break DICLEGIS tablets before swallowing. If you cannot swallow DICLEGIS tablets whole, tell your healthcare provider.
- If you take too much DICLEGIS (overdose), you may have the following symptoms: restlessness, dry mouth, the pupils of your eyes become larger (dilated), sleepiness, dizziness, confusion, fast heart rate, seizures, muscle pain or weakness, and sudden and severe kidney problems. If you have these symptoms and they are severe, they may lead to death. Stop taking DICLEGIS, call your healthcare provider or go to the nearest hospital emergency room right away. For more information about overdose treatment, call your poison control center at 1-800-222-1222.

What are the possible side effects of DICLEGIS?

DICLEGIS may cause serious side effects, including drowsiness.

Drowsiness is a common side effect when taking DICLEGIS, but can also be severe:

- Do not drive, operate heavy machinery, or other activities that need your full attention unless your healthcare provider says that you may do so.
- Do not drink alcohol, or take other central nervous system depressants such as cough and cold medicines, certain pain medicines, and medicines that help you sleep while you take DICLEGIS. Severe drowsiness can happen or become worse causing falls or accidents.

DICLEGIS may cause false positive urine drug screening test for methadone, opiates and PCP.

These are not all the possible side effects of DICLEGIS.

Call your doctor for medical advice about side effects. You may report side effects to FDA at 1-800-FDA-1088.

How should I store DICLEGIS?

- Store DICLEGIS between 68°F to 77°F (20°C to 25°C).
- Keep DICLEGIS tablets dry, in a tightly closed container, and out of the light.
- Safely throw away medicine that is out of date or no longer needed.

Keep DICLEGIS and all medicines out of the reach of children.

General information about the safe and effective use of DICLEGIS.

Medicines are sometimes prescribed for purposes other than those listed in a Patient Information leaflet. You can ask your pharmacist or healthcare provider for information about DICLEGIS that is written for health professionals. Do not use DICLEGIS for a condition for which it was not prescribed. Do not give DICLEGIS to other people, even if they have the same symptoms that you have. It may harm them.

What are the ingredients in DICLEGIS?

Active ingredient: doxylamine succinate (an antihistamine) and pyridoxine hydrochloride (vitamin B6).

Inactive ingredients: ammonium hydroxide, n-butanol, carnauba wax powder, colloidal silicon dioxide, croscarmellose sodium, D&C Red#27, denatured alcohol, FD&C Blue #2, hypromellose, isopropyl alcohol, magnesium stearate, magnesium trisilicate, methacrylic acid copolymer, microcrystalline cellulose 102, PEG 400, PEG 8000, polysorbate 80, propylene glycol, shellac glaze, simethicone, sodium bicarbonate, sodium lauryl sulfate, talc, titanium dioxide, triethyl citrate.

Distributed by: Duchesnay USA, Inc., Princeton, NJ 08540,
www.duchesnayusa.com or call 1-855-722-7734.

This Patient Information has been approved by the U.S. Food and Drug Administration Issued: June 2023

Package/Label Display Panel

Bottle Label-Outside Front Cover with Imprint Area for Lot & Expiry

Bottle Label – Inside Cover